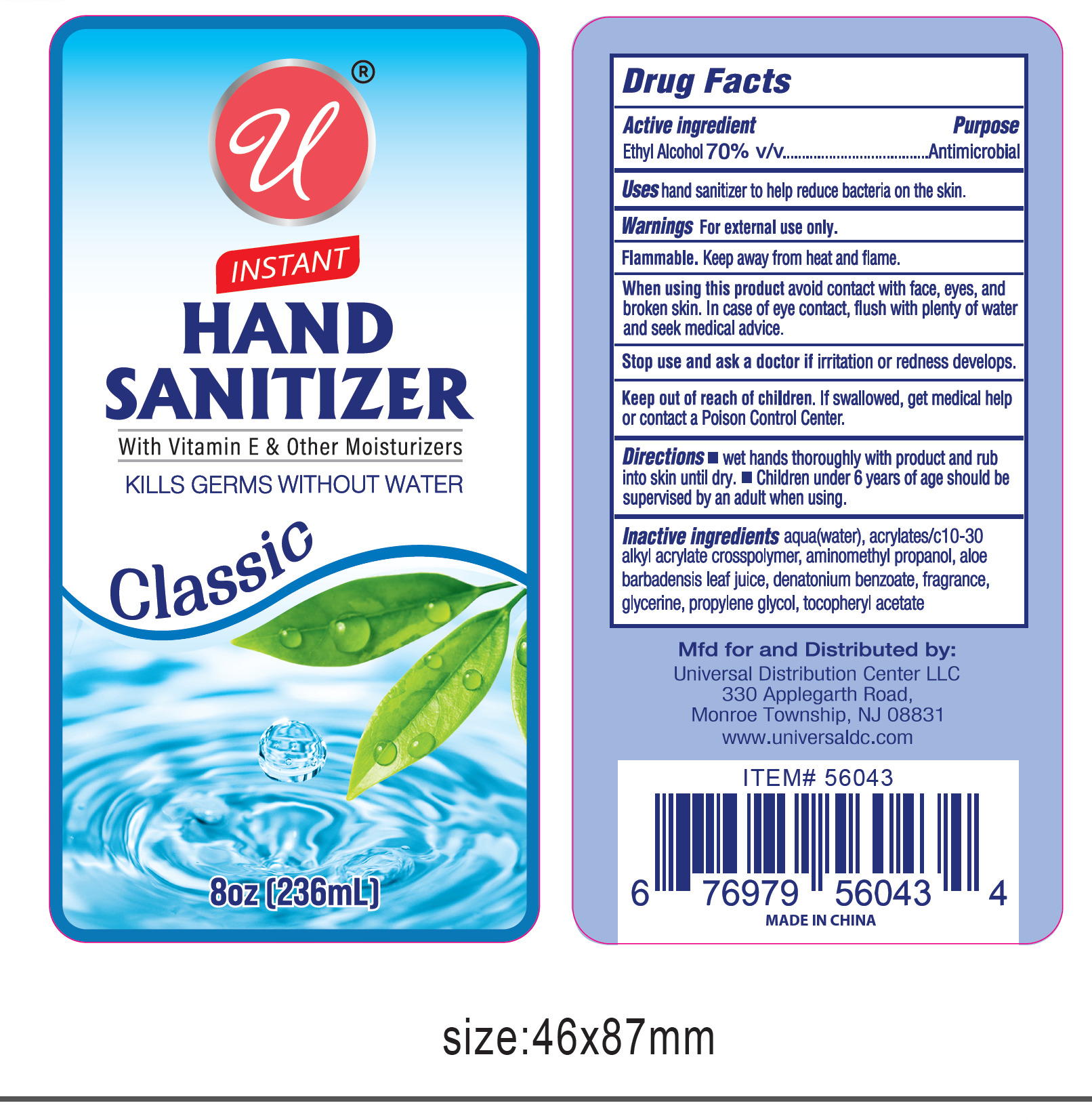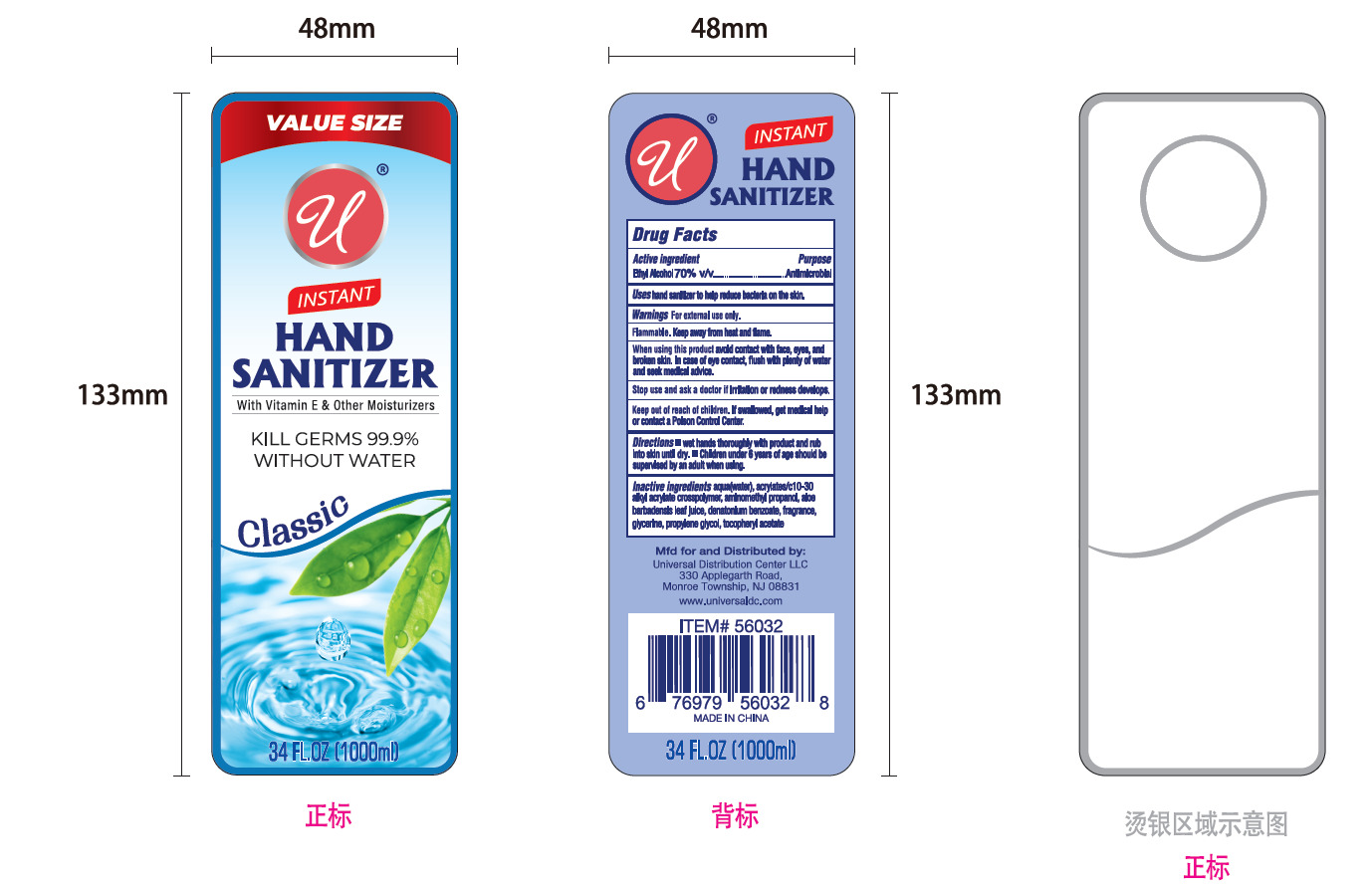 DRUG LABEL: INSTANT HAND SANITIZER
NDC: 75541-016 | Form: LIQUID
Manufacturer: NINGBO MEITELI COSMETICS CO., LTD
Category: otc | Type: HUMAN OTC DRUG LABEL
Date: 20260202

ACTIVE INGREDIENTS: ALCOHOL 70 mL/100 mL
INACTIVE INGREDIENTS: TANGERINE PEEL; AQUA; ACRYLATES/C10-30 ALKYL ACRYLATE CROSSPOLYMER (60000 MPA.S); GLYCERIN; PROPYLENE GLYCOL; DENATONIUM BENZOATE; ALPHA-TOCOPHEROL ACETATE; ALOE BARBADENSIS LEAF JUICE; AMINOMETHYL PROPANOL

75541-016

Active Ingredient(s)

ETHYL ALCOHOL：70%

Purpose

Antimicrobial

Use

Uses hand sanitizer to help reduce bacteria on the skin.

Warnings

Warnings For external use only.

Do not use

Children under two years old, please do not use

When using this product avoid contact with face, eyes, and
broken skin. In case of eye contact, flush with plenty of water
and seek medical advice.

Stop use and ask a doctor if irritation or redness develops.

Keep out of reach of children. If swallowed, get medical help
or contact a Poison Control Center.

Directions

Directions ■ wet hands thoroughly with product and rub
into skin until dry. ■Children under 6 years of age should be
supervised by an adult when using.

Other information

Flammable. Keep away from heat and flame.

Inactive ingredients

Inactive ingredients aqua(water), acrylates/c10-30
alkyl acrylate crosspolymer, aminomethyl propanol, aloe
barbadensis leaf juice, denatonium benzoate, fragrance,
glycerine, propylene glycol, tocopheryl acetate